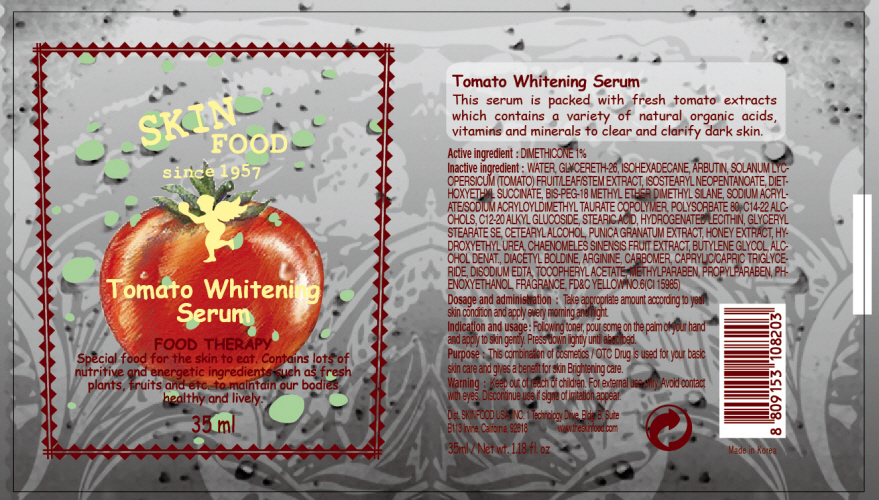 DRUG LABEL: TOMATO WHITENING SERUM
NDC: 76214-005 | Form: CREAM
Manufacturer: SKINFOOD CO., LTD.
Category: otc | Type: HUMAN OTC DRUG LABEL
Date: 20110721

ACTIVE INGREDIENTS: DIMETHICONE 0.35 mL/35 mL
INACTIVE INGREDIENTS: WATER; GLYCERETH-26; ISOHEXADECANE; ARBUTIN; POLYSORBATE 80; C14-22 ALCOHOLS; C12-20 ALKYL GLUCOSIDE; STEARIC ACID; METHYLPARABEN; HYDROGENATED SOYBEAN LECITHIN; CETOSTEARYL ALCOHOL; POMEGRANATE; PROPYLPARABEN; PHENOXYETHANOL; HONEY; HYDROXYETHYL UREA; CHAENOMELES SPECIOSA FRUIT; BUTYLENE GLYCOL; ARGININE; EDETATE DISODIUM

Drug Facts

Active ingredient: DIMETHICONE

Inactive ingredients:

WATER, GLYCERETH-26, ISOHEXADECANE, ARBUTIN, SOLANUM LYCOPERSICUM (TOMATO) FRUIT/LEAF/STEM EXTRACT, ISOSTEARYL NEOPENTANOATE, DIETHOXYETHYL SUCCINATE, BIS-PEG-18 METHYL ETHER DIMETHYL SILANE, SODIUM ACRYLATE/SODIUM ACRYLOYLDIMETHYL TAURATE COPOLYMER, POLYSORBATE 80, C14-22 ALCOHOLS, C12-20 ALKYL GLUCOSIDE, STEARIC ACID, HYDROGENATED LECITHIN, GLYCERYL STEARATE SE, CETEARYL ALCOHOL, PUNICA GRANATUM EXTRACT, HONEY EXTRACT, HYDROXYETHYL UREA, CHAENOMELES SINENSIS FRUIT EXTRACT, BUTYLENE GLYCOL, ALCOHOL DENAT., DIACETYL BOLDINE, ARGININE, CARBOMER, CAPRYLIC/CAPRIC TRIGLYCERIDE, DISODIUM EDTA, TOCOPHERYL ACETATE, METHYLPARABEN, PROPYLPARABEN, PHENOXYETHANOL, FRAGRANCE

Purpose:

This combination of cosmetics is used for your basic skin care and gives a benefit for skin Brightening care.

Warnings:

For external use only. Avoid contact with eyes. Discontinue use if signs of irritation appear.

Keep out of reach of children:

Keep out of reach of children

Indication and usage:

Following toner, pour some on the palm of your hand and apply to skin gently. Press down lightly until absorbed.

Dosage and administration:

Take appropriate amount according to your skin condition and apply every morning and night.